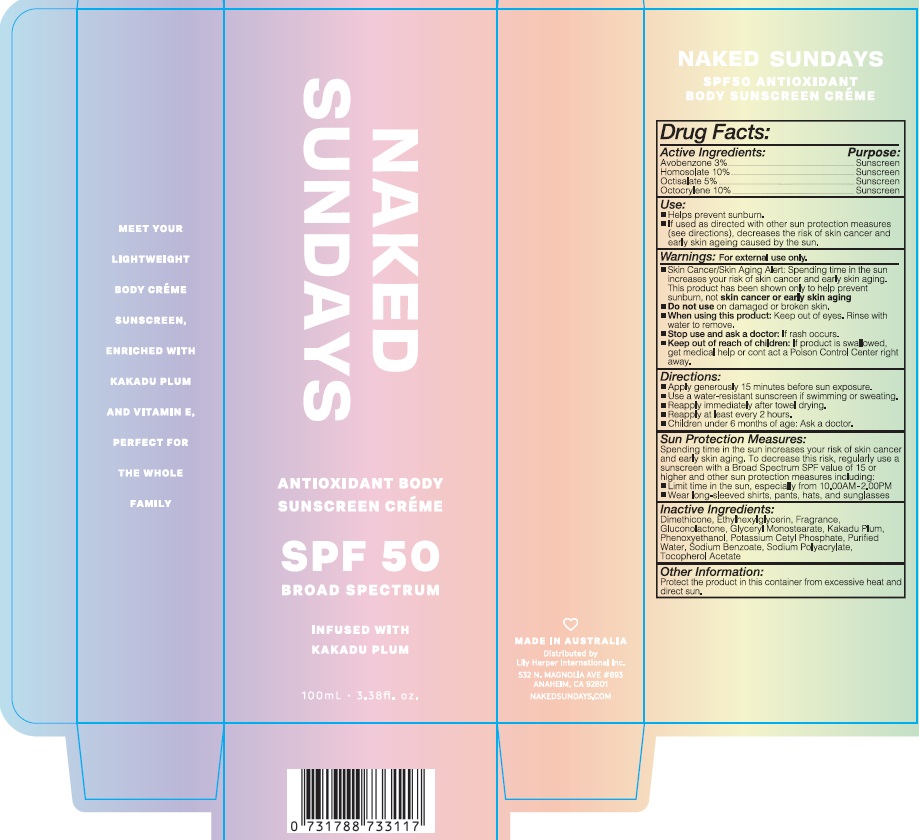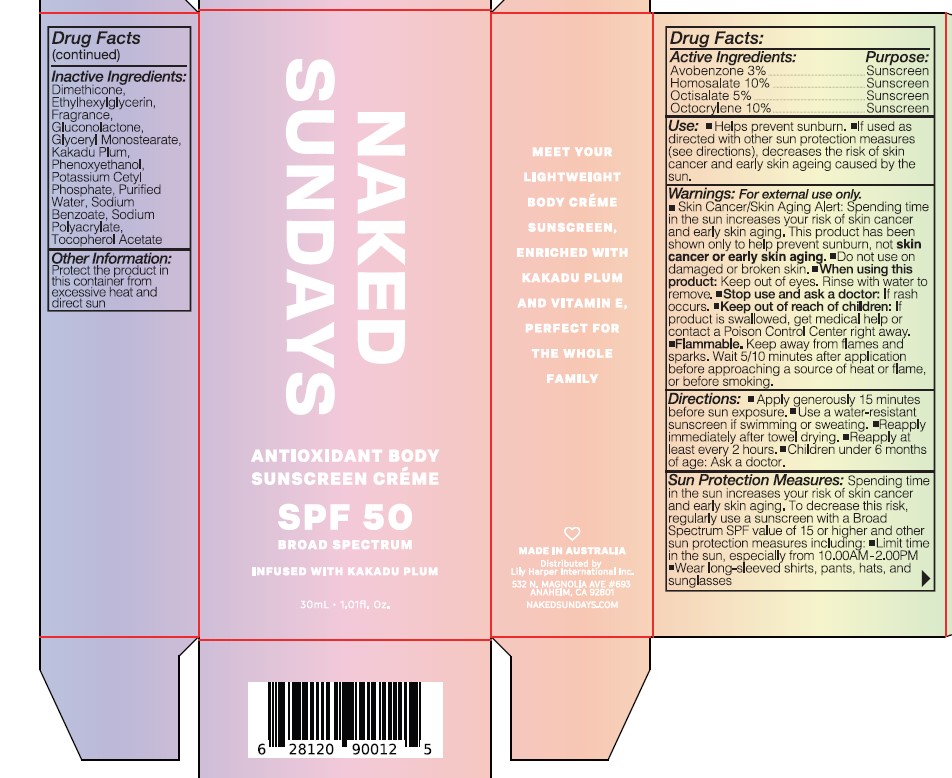 DRUG LABEL: ANTIOXIDANT BODY SUNSCREEN CREME SPF50 BROAD SPECTRUM
NDC: 81104-900 | Form: OIL
Manufacturer: NAKED SUNDAY PTY LTD
Category: otc | Type: HUMAN OTC DRUG LABEL
Date: 20250323

ACTIVE INGREDIENTS: HOMOSALATE 10 g/100 mL; OCTISALATE 5 g/100 mL; OCTOCRYLENE 10 g/100 mL; AVOBENZONE 3 g/100 mL
INACTIVE INGREDIENTS: ALPHA-TOCOPHEROL ACETATE; DIMETHICONE; POTASSIUM CETYL PHOSPHATE; GLYCERYL MONOSTEARATE; PHENOXYETHANOL; ETHYLHEXYLGLYCERIN; SODIUM BENZOATE; KAKADU PLUM; GLUCONOLACTONE; SODIUM POLYACRYLATE (8000 MW); WATER

NAKED SUNDAYS ANTIOXIDANT BODY SUNSCREEN CRÈME SPF 50 BROAD SPECTRUM

ACTIVE INGREDIENTS

AVOBENZONE 3 %

HOMOSALATE 10%

OCTISALATE 5 %

OCTOCRYLENE 10%

PURPOSE

SUNSCREEN

USE

- Helps prevents sunburn

- If used as directed with other sun protection measures (see directions) decreases the risk of skin cancer and early skin ageing caused by the sun.

WARNINGS

FOR EXTERNAL USE ONLY

- Do not use on damaged or broken skin.

Skin Cancer/Skin Aging Alert: Spending time in the sun
increases your risk of skin cancer and early skin aging.
This product has been shown only to help prevent
sunburn, not skin cancer or early skin aging

WHEN USING

keep out of eyes, Rinse with water to remove

Stop use & ask doctor

If rash occurs

KEEP OUT OF REACH OF CHILDREN

If product is swallowed , get medical help or contact a poison control center right away

Directions

Apply generously 15 minutes before sun exposure.
Use a water-resistant sunscreen if swimming or sweating.
Reapply immediately after towel drying.
Reapply at least every 2 hours.
Children under 6 months of age: Ask a doctor.

Sun Protection Measures :

Spending time in the sun increases your risk of skin cancer and early skin aging. To decrease this risk, regularly use a sunscreen with a Broad spectrum SPF value of 15 or higher and other sun protection measures inclusing:

- limit time in the sun, especially from 10:00 AM- 02:00 PM

- Wear long- Sleeved shirts , pants, Hats and sunglasses

Inactive Ingredients

Dimethicone, Ethylhexylglycerin, Fragrance, Gluconolactone,
Glyceryl Monostearate, Kakadu Plum, Phenoxyethanol,
Potassium Cetyl Phosphate, Purified Water, Sodium
Benzoate, Sodium Polyacrylate, Tocopherol acetate

OTHER SAFETY INFORMATION

Protect the product in this container from excessive heat & direct sun

Dosage and Administration

For External use Only, Apply over skin